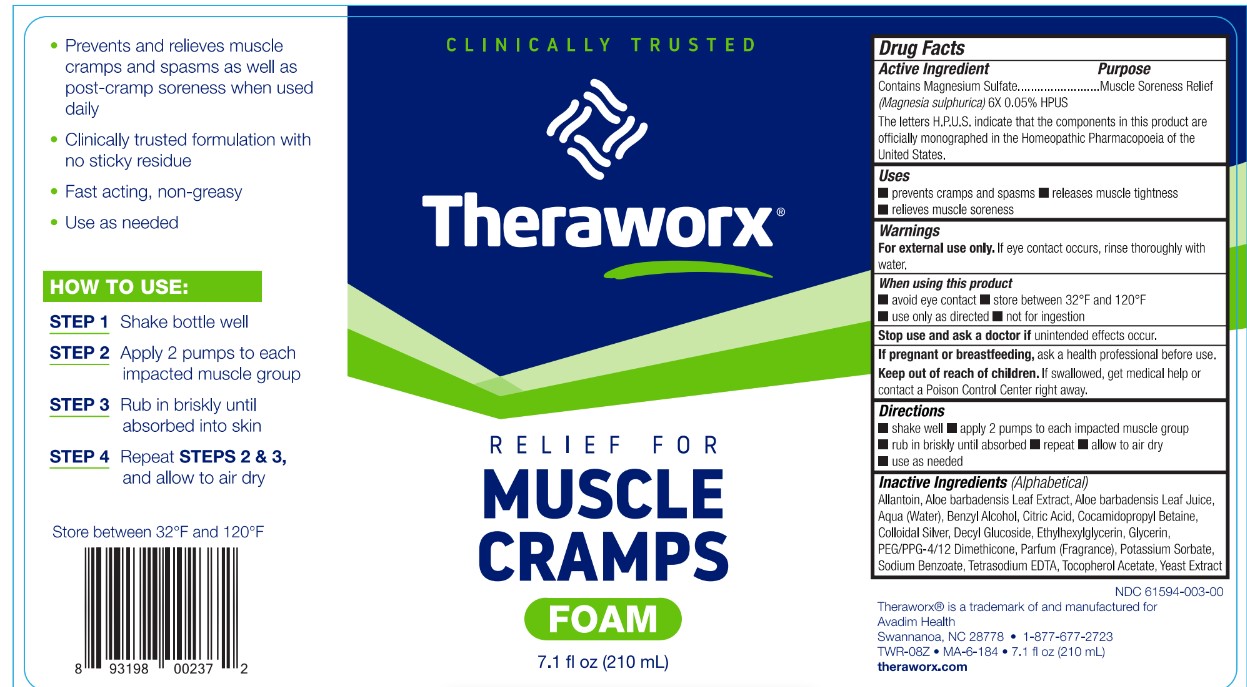 DRUG LABEL: Theraworx Relief Muscle Cramp and Spasm Relief
NDC: 61594-003 | Form: AEROSOL, FOAM
Manufacturer: AVADIM HOLDINGS, INC.
Category: homeopathic | Type: HUMAN OTC DRUG LABEL
Date: 20240701

ACTIVE INGREDIENTS: MAGNESIUM SULFATE HEPTAHYDRATE 6 [hp_X]/210 mL
INACTIVE INGREDIENTS: WATER; COCAMIDOPROPYL BETAINE; ALOE VERA LEAF; SILVER; .ALPHA.-TOCOPHEROL ACETATE; GLYCERIN; ALLANTOIN; GRAPEFRUIT; LAURYL GLUCOSIDE; EDETATE SODIUM; PEG/PPG-4/12 DIMETHICONE; METHYLPARABEN; PROPYLPARABEN

Theraworx Relief Muscle Cramp and Spasm Relief Foam

Active Ingredient

Contains Magnesium Sulfate (Magnesia sulphurica) 6X 0.05% HPUS The letters H.P.U.S. indicate that the components in this product are officially monographed in the Homeopathic Pharmacopoeia of the United States.

Purpose

Muscle Soreness Relief

Uses

- prevents muscle cramps
- releases muscle tightness
- reduces muscle soreness

Warnings

For external use only. If eye contact occurs, rinse thoroughly with water.

When using this product

• avoid eye contact • do not store at temperature above 120°F • use only as directed • not for ingestion

Stop use and ask a doctor if

unintended effects occur.

If pregnant or breastfeeding,

ask a health professional before use.

Keep out of reach of children.

If swallowed, get medical help or contact a Poison Control Center right away.

Directions

• shake well • apply 2 pumps onto entire muscle group(s) or area • briskly rub in until absorbed • use as needed • allow to air dry

Inactive Ingredients

Aqua (Water), Cocamidopropyl Betaine, Aloe Barbadensis Leaf Juice, Colloidal Silver, Tocopheryl Acetate, Glycerin, Allantoin, Beta Glucan, Citrus Paradisi (Grapefruit) Fruit Extract, Lauryl Glucoside, Tetrasodium EDTA, PEG/PPG-4/12 Dimethicone, Methylparaben, Propylparaben, Parfum (Fragrance)